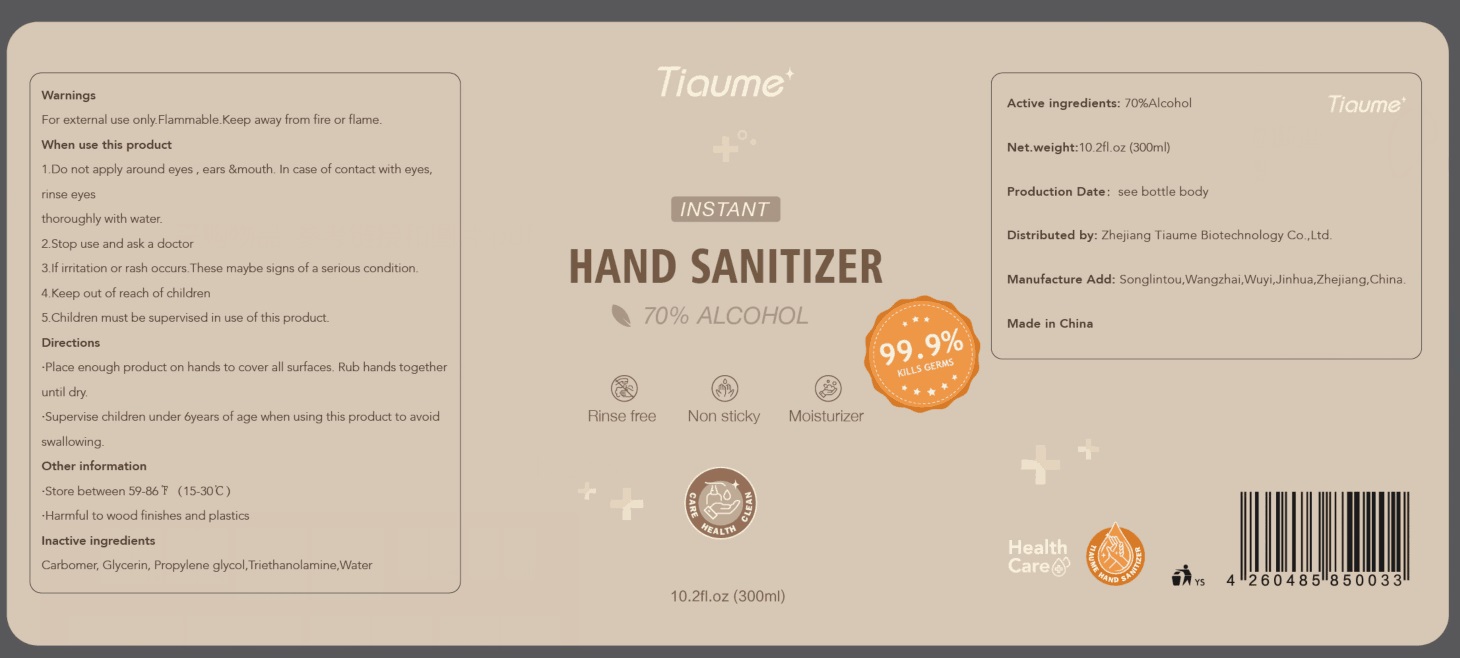 DRUG LABEL: Hand sanitizer
NDC: 80915-001 | Form: GEL
Manufacturer: Zhejiang Tiaume Biotechnology Co., Ltd.
Category: otc | Type: HUMAN OTC DRUG LABEL
Date: 20201104

ACTIVE INGREDIENTS: ALCOHOL 70 mL/100 mL
INACTIVE INGREDIENTS: CARBOMER HOMOPOLYMER, UNSPECIFIED TYPE; WATER; GLYCERIN; PROPYLENE GLYCOL; TROLAMINE

80915-001
Hand sanitizer

Active Ingredient(s)

ALCOHOL 70% v/v

Purpose

Antiseptic

Use

Place enough product on hands to cover all surfaces. Rub hands together until dry.
Supervise children under 6years of age when using this product to avoid swallowing.

Warnings

For external use only.Flammable.Keep away from fire or flame.

When use this product

Do not apply around eyes, ears &mouth. In cuse of contact with eyes, rinse eyes thoroughly with water.

Stop use and ask a doctor lf irntation or rash occurs.These maybe signs of a serious condition.

Keep out of reach of children, Children must be supervised in use of this product.

Do not use

Do not apply around eyes, ears &mouth. In cuse of contact with eyes, rinse eyes thoroughly with water.

When use this product

Do not apply around eyes, ears &mouth. In cuse of contact with eyes, rinse eyes thoroughly with water.

Stop use and ask a doctor lf irntation or rash occurs.These maybe signs of a serious condition.

Keep out of reach of children, Children must be supervised in use of this product.

Stop use and ask a doctor lf irntation or rash occurs.These maybe signs of a serious condition.

Keep out of reach of children, Children must be supervised in use of this product.

Directions

Place enough product on hands to cover all surfaces. Rub hands together until dry.
Supervise children under 6years of age when using this product to avoid swallowing.

Other information

Store between 59-86F(15-30C)
Harmful to wood finishes and plastics

Inactive ingredients

Carbomer, Glycerin, Propylene glycol,Triethanolamine,Water